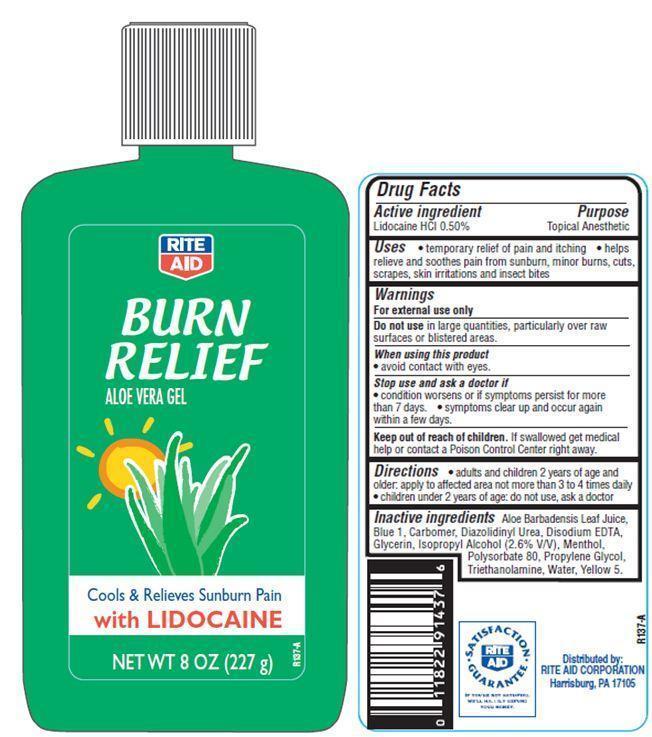 DRUG LABEL: Rite Aid Burn Relief
NDC: 11822-9009 | Form: GEL
Manufacturer: RITE AID CORPORATION
Category: otc | Type: HUMAN OTC DRUG LABEL
Date: 20121203

ACTIVE INGREDIENTS: LIDOCAINE HYDROCHLORIDE 0.5 g/100 g
INACTIVE INGREDIENTS: WATER; TROLAMINE; ISOPROPYL ALCOHOL; EDETATE DISODIUM; ALOE VERA LEAF; PROPYLENE GLYCOL; GLYCERIN; POLYSORBATE 80; DIAZOLIDINYL UREA; MENTHOL; FD&C BLUE NO. 1; FD&C YELLOW NO. 5

Drug Facts

Active Ingredient

Lidocaine HCl 0.50%

Purpose

Topical Anesthetic

Uses

- temporary pain relief of pain and itching
- helps relieve and soothes pain from sunburn, minor burns, cuts, scrapes, skin irritations and insect bites.

Warnings

For external use only

Do not use in large quantities, particularly over raw surfaces or blistered areas.

When using this product

- avoid contact with eyes.

Stop use and ask a doctor if

- Conditions worsens or if symptoms persists for more than 7 days.
- Symptoms clear up and occur again within a few days.

Keep out of reach of children.

If swallowed get medical help or contact a Poison Control Center right away.

Directions

- adults and children 2 years of age and older.apply to affected area not more than 3 to 4 times daily
- children under 2 years of age: do not use, ask a doctor.

Inactive Ingredients

Aloe Barbadensis Leaf Juice, Water, Propylene Glycol, Glycerin, Isopropyl Alcohol, Triethanolamine, Polysorbate 80, Carbomer, Diazolidinyl urea, Disodium EDTA, Menthol, Yellow 5, Blue 1.

Principal Display Panel

RITE AID
BURN RELIEF
ALOE VERA GEL
Cools and Relieves Sunburn Pain
with LIDOCAINE
NET WT 8 OZ (227 g)